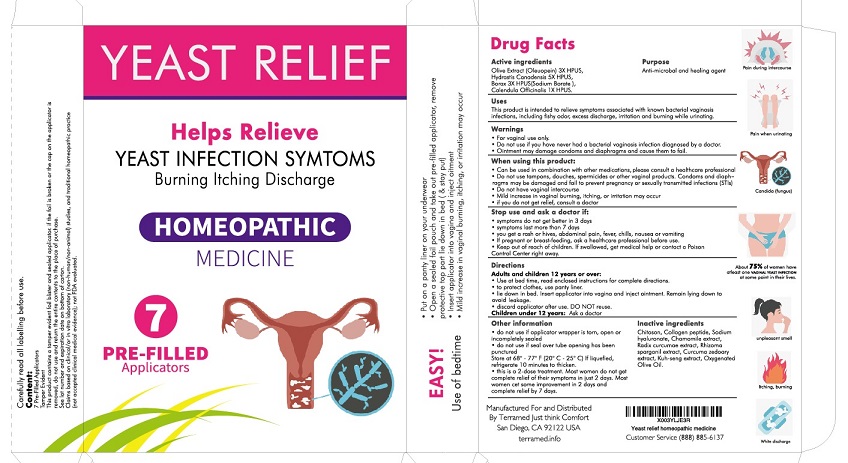 DRUG LABEL: Terramed Just Think Comfort Yeast relief
NDC: 83004-004 | Form: GEL
Manufacturer: Rida LLC
Category: homeopathic | Type: HUMAN OTC DRUG LABEL
Date: 20250225

ACTIVE INGREDIENTS: OLEUROPEIN 3 [hp_X]/100 mL; GOLDENSEAL 5 [hp_X]/100 mL; SODIUM BORATE 3 [hp_X]/100 mL; CALENDULA OFFICINALIS FLOWERING TOP 1 [hp_X]/100 mL
INACTIVE INGREDIENTS: POLIGLUSAM; POVIDONE-IODINE; SODIUM; CHAMAEMELUM NOBILE FLOWER; CURCUMA KWANGSIENSIS ROOT; SPARGANIUM STOLONIFERUM ROOT; CURCUMA ZEDOARIA WHOLE; OLIVE OIL

Drug Facts

Active Ingredient

Olive Extract (oleuropein) 3X HPUS
Hydrastis Canadensis 5X HPUS
Borax (Sodium Borate) 3X HPUS
Calendula Officinalis 1X HPUS

Purpose

Anti-microbial and Healing agent

Uses

This product is intended to relieve symptoms associated with known yeast infections, including fishy odor, excess discharge, irritation and burning while urinating.

Warnings

- For vaginal use only.
- Do not use if you have never had vaginal infection diagnosed by a doctor.
- Ointment may damage condoms and diaphragms and cause them to fail.

Ask a doctor before use if you have:

- vaginal itching and discomfort for the first time
- lower abdominal, back or shoulder pain, fever, chills, nausea, vomiting or foul-smelling vaginal discharge. You may have a more serious condition.
- bacterial vaginosis often (such as once a month or 3 in 6 months). You could be pregnant or have a serious underlying medical cause for your symptoms, including diabetes or a weakened immune system.
- been exposed to the human immunodeficiency virus (HIV) that causes AIDS.
- Do not use if you are allergic to any ingredient in this product

When using this product

- do not use tampons, douches, spermicides or other vaginal products. Condoms and diaphragms may be damaged and fail to prevent pregnancy or sexually transmitted infections (STIs)
- do not have vaginal intercourse
- mild increase in vaginal burning, itching, or irritation may occur
- if you do not get relief, consult a doctor

Stop use and ask a doctor if
• symptoms do not get better in 3 days
• symptoms last more than 7 days
• you get a rash or hives, abdominal pain, fever, chills, nausea or vomiting

- If pregnant or breast-feeding ask a healthcare professional before use.
- Keep out of the reach of children If swallowed, get medical help or contact Poison Control Center right away

Directions

For individuals aged 12 and older:

- Utilize this product before bedtime; refer to the enclosed instructions for comprehensive guidance.
- Place a panty liner in your underwear to prevent any potential leakage.
- While lying in bed, gently insert the applicator into the vagina and administer the ointment. Stay in a reclined position to minimize the risk of leakage.
- Dispose of the applicator after a single use.

Children under 12 years: Ask a doctor

Inactive Ingredients

Chitosan, povidone-iodine, Sodium hyaluonate, Chammomile Extract, Radix Curcumae extract, Rhizoma Sparganil extract, Curcuma zedoary extract, Kuh-seng extract, Oxygenated olive oil

Other information

• Avoid usage if the applicator wrapper is damaged, opened, or not fully sealed.
• Do not use if the seal over the tube opening has been pierced.
• Store between 68°-77°F (20°C - 25°C). If the product liquefies, refrigerate it for 10 minutes to regain its thickness

Please note that this treatment consists of 7 doses. While many women may not experience complete symptom relief within just two days, most will notice some improvement in that timeframe and should expect complete relief within seven days.